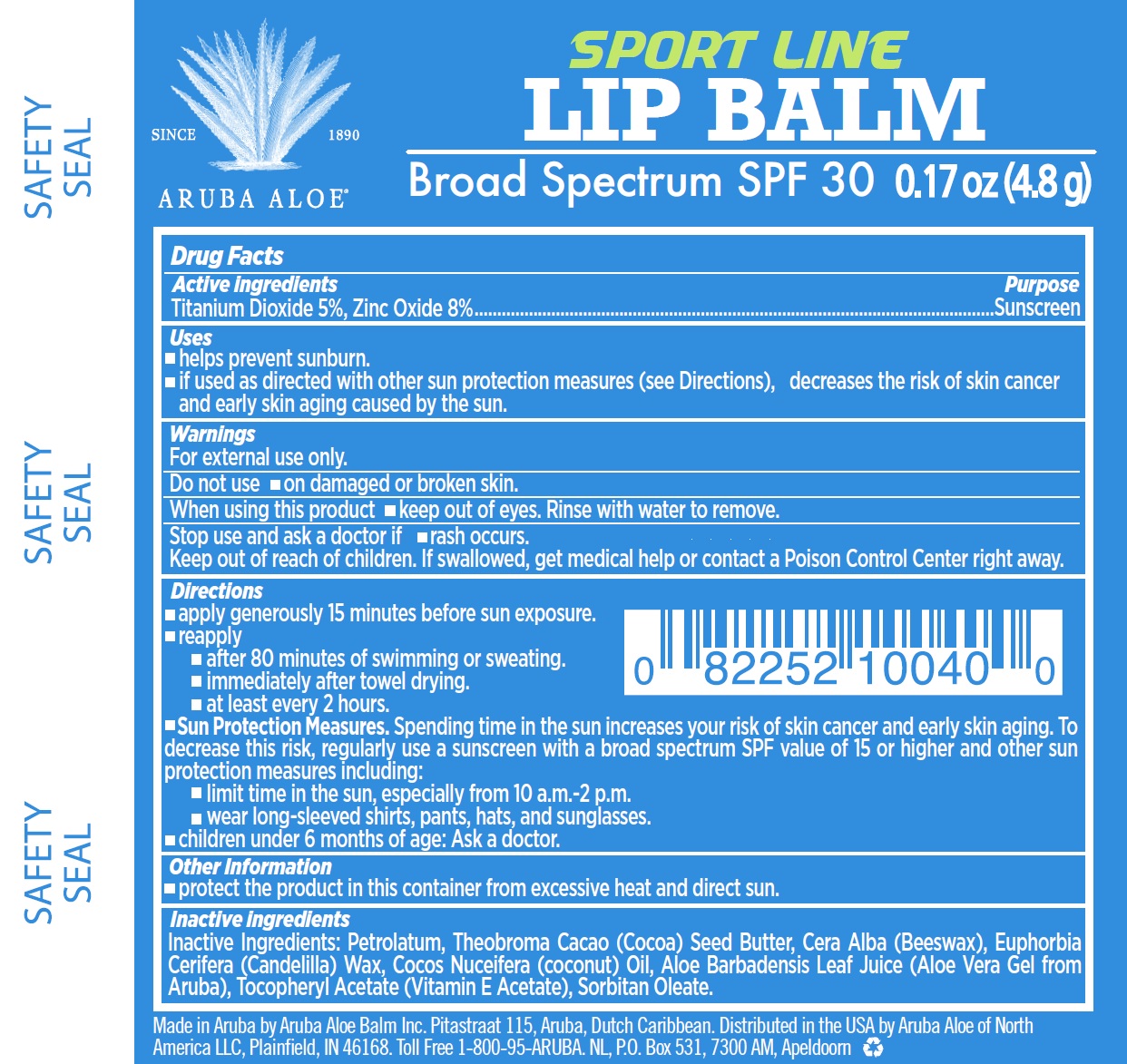 DRUG LABEL: Aruba Aloe Sport Line Lip Balm Broad Spectrum SPF 30
NDC: 53675-187 | Form: STICK
Manufacturer: Aruba Aloe Balm NV
Category: otc | Type: HUMAN OTC DRUG LABEL
Date: 20231106

ACTIVE INGREDIENTS: TITANIUM DIOXIDE 50 mg/1 g; ZINC OXIDE 80 mg/1 g
INACTIVE INGREDIENTS: PETROLATUM; COCOA; WHITE WAX; CANDELILLA WAX; COCONUT OIL; ALOE VERA LEAF; .ALPHA.-TOCOPHEROL ACETATE; SORBITAN MONOOLEATE

Aruba Aloe Sport Line Lip Balm Broad Spectrum SPF 30

Active ingredients

Titanium Dioxide 10% Zinc Oxide 10%

Purpose

Sunscreen

Uses

- helps prevent sunburn.
- if used as directed with other sun protection measures (see Directions), decreases the risk of skin cancer and early skin aging caused by the sun.

Warnings

For external use only.

Do not use

- on damaged or broken skin.

When using this product

- keep out of eyes. Rinse with water to remove.

Stop use and ask a doctor if

- rash occurs.

Keep out of reach of children.

f swallowed, get medical help or contact a Poison Control Center right away.

Directions

- apply generously 15 minutes before sun exposure.
- reapply
- after 80 minutes of swimming or sweating.
- immediately after towel drying.
- at least every 2 hours.
- Spending time in the sun increases your risk of skin cancer and early skin aging. To decrease this risk, regularly use a sunscreen with a broad spectrum SPF value of 15 or higher and other sun protection measures including: Sun Protection Measures.
- limit time in the sun, especially from 10 a.m.-2 p.m.
- wear long-sleeved shirts, pants, hats, and sunglasses.
- children under 6 months of age: Ask a doctor.

Other Information

- protect the product in this container from excessive heat and direct sun.

Inactive ingredients

Petrolatum, Theobroma Cacao (Cocoa) Seed Butter, Cera Alba (Beeswax), Euphorbia Cerifera (Candelilla) Wax, Cocos Nuceifera (coconut) Oil, Aloe Barbadensis Leaf Juice (Aloe Vera Gel from Aruba), Tocopheryl Acetate (Vitamin E Acetate), Sorbitan Oleate.